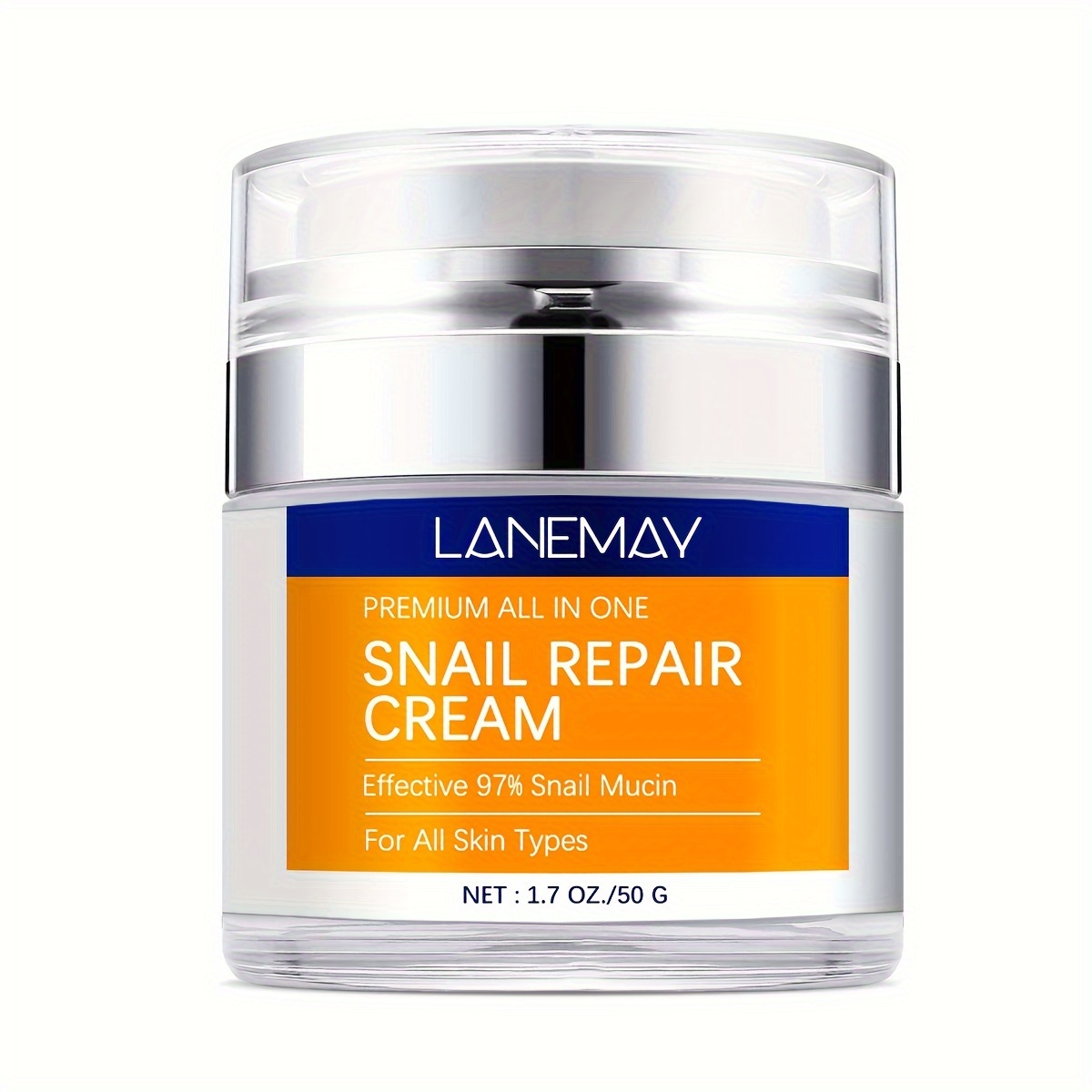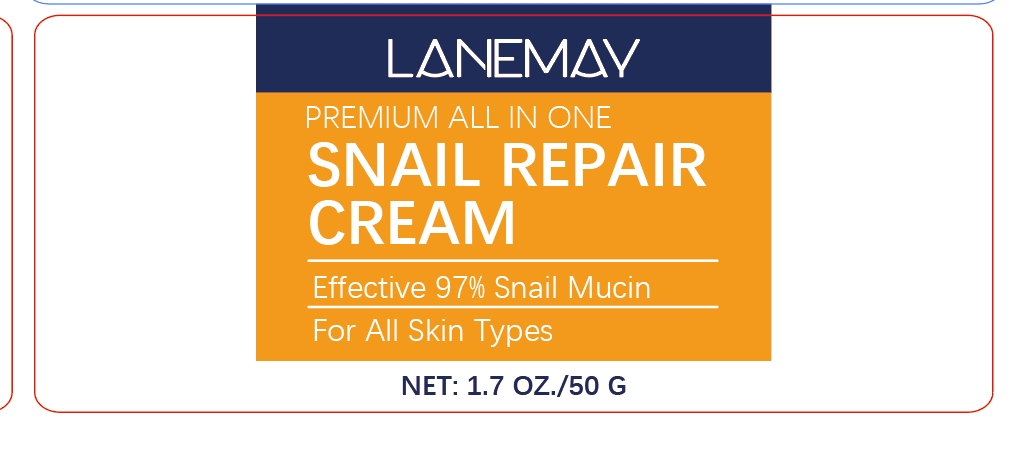 DRUG LABEL: Snail Repair Cream
NDC: 84025-032 | Form: CREAM
Manufacturer: Guangzhou Yanxi Biotechnology Co., Ltd
Category: otc | Type: HUMAN OTC DRUG LABEL
Date: 20240406

ACTIVE INGREDIENTS: SQUALANE 3 mg/50 mL; GLYCERIN 2 mg/50 mL
INACTIVE INGREDIENTS: WATER

DOSAGE AND ADMINISTRATION

use as a normal facial cream

INACTIVE INGREDIENT

Aqua

INDICATIONS AND USAGE

Apply to affected area twice per day on cleansed skin.

keep out of reach of children.

WARNINGS

For external use only.

PURPOSE

Hydrate, Renew and Protect Skin